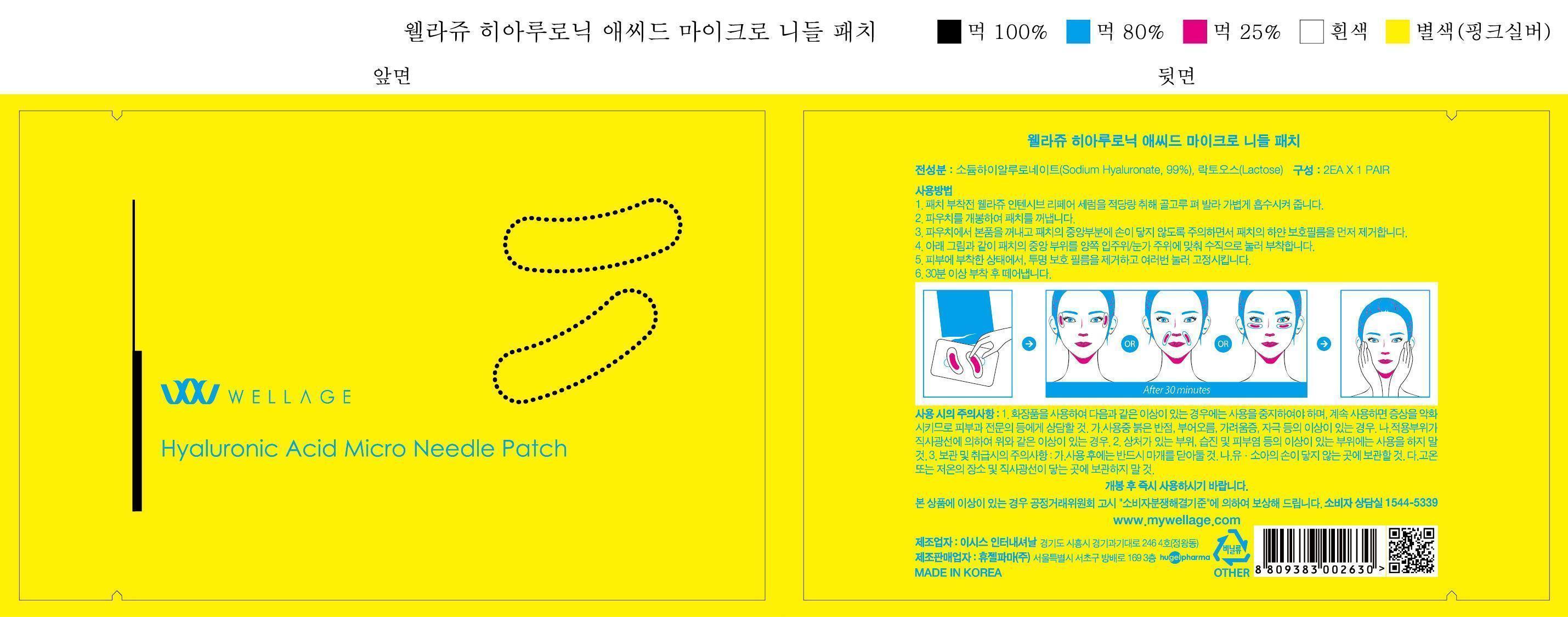 DRUG LABEL: WELLAGE Hyaluronic Acid Micro Needle
NDC: 69346-9001 | Form: PATCH
Manufacturer: HUGEL PHARMA CO.,LTD
Category: otc | Type: HUMAN OTC DRUG LABEL
Date: 20150530

ACTIVE INGREDIENTS: HYALURONIC ACID 99 g/100 g
INACTIVE INGREDIENTS: LACTOSE

Drug Facts

ACTIVE INGREDIENT

niacinamide, panthenol

INACTIVE INGREDIENT

■Zinc pyrithion suspention ■Di-Water ■Lauryl glucoside ■Glycerin ■Sophora Root EXT ■Licorice Root EXT ■Panax Ginseng Root EXT ■Cnidium Root EXT ■Sage plant Root EXT ■Aloe EXT ■Angelica Gigas Root EXT ■Mugwort EXT ■Greentea EXT ■Ginkgo leaf EXT ■Beer yeast EXT ■Copper peptide ■I-Menthol ■Xanthan gum ■Acorus Calamus Root EXT ■Methylparaben ■Flavor ■Chinese pepper EXT ■Mugwort EXT ■Greentea EXT ■Ginkgo leaf EXT ■Propyl p-Hydroxybenzoate

PURPOSE

scalp protectant (hair growth and loss prevention)

keep out of reach of the children

INDICATIONS AND USAGE

■Wet hair with worm water
■Apply the shampoo work into a rich lather
■Massage thoroughly into the hair and scalp
■Rinse well and repeat to maximize results

WARNINGS

■store between 20-25 °C (68-77 °F)
■avoid freezing and excessive heat above 40 °C (104 °F)

DOSAGE AND ADMINISTRATION

If contact occurs, rinse with plenty of worm or cold water right away and in a serious situation, contact a physician. If swallowing, drink plenty of water and contact a physician